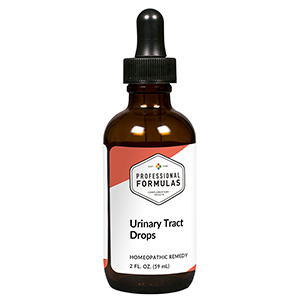 DRUG LABEL: Urinary Tract Drops
NDC: 63083-2122 | Form: LIQUID
Manufacturer: Professional Complementary Health Formulas
Category: homeopathic | Type: HUMAN OTC DRUG LABEL
Date: 20190815

ACTIVE INGREDIENTS: CRATEVA MAGNA BARK 3 [hp_X]/59 mL; AGATHOSMA BETULINA LEAF 6 [hp_X]/59 mL; SUS SCROFA URINARY BLADDER 6 [hp_X]/59 mL; EQUISETUM ARVENSE TOP 6 [hp_X]/59 mL; BEEF KIDNEY 6 [hp_X]/59 mL; TOXICODENDRON PUBESCENS LEAF 12 [hp_X]/59 mL; SEPIA OFFICINALIS JUICE 60 [hp_X]/59 mL; DELPHINIUM STAPHISAGRIA SEED 60 [hp_X]/59 mL; LYTTA VESICATORIA 12 [hp_X]/59 mL; SMILAX ORNATA ROOT 12 [hp_X]/59 mL; CAUSTICUM 30 [hp_X]/59 mL; CHIMAPHILA UMBELLATA WHOLE 30 [hp_X]/59 mL; URTICA URENS WHOLE 30 [hp_X]/59 mL
INACTIVE INGREDIENTS: ALCOHOL; WATER

C122

ACTIVE INGREDIENTS

Crataeva 3X
Barosma 6X
Bladder 6X
Equisetum arvense 6X
Kidney 6X
Rhus toxicodendron 12X
Sepia 60X
Staphysagria 60X
Cantharis 12C
Sarsaparilla 12C
Causticum 30C
Chimaphila umbellata 30C
Urtica urens 30C

QUESTIONS

Professional Formulas

PO Box 2034 Lake Oswego, OR 97035

INDICATIONS

For the temporary relief of urinary discomfort or difficulty, frequent urination, or mild abdominal or back pain.*

PURPOSE

*Claims based on traditional homeopathic practice, not accepted medical evidence. Not FDA evaluated.

WARNINGS

Consult a doctor if condition worsens, if symptoms persist, or are accompanied by a fever or bloody or cloudy urine. Keep out of the reach of children. In case of overdose, get medical help or contact a poison control center right away. If pregnant or breastfeeding, ask a healthcare professional before use.

Keep out of the reach of children.

PREGNANCY OR BREAST FEEDING

If pregnant or breastfeeding, ask a healthcare professional before use.

DIRECTIONS

Place drops under tongue 30 minutes before/after meals. Adults and children 12 years and over: Take 10 drops up to 3 times per day. Consult a physician for use in children under 12 years of age.

OTHER INFORMATION

Tamper resistant. If seal is broken, do not use. After opening, close container tightly and store at room temperature away from heat.

INACTIVE INGREDIENTS

20% ethanol, purified water.

LABEL

Est 1985

Professional Formulas

Complementary Health

Urinary Tract Drops

Homeopathic Remedy

2 FL. OZ. (59 mL)